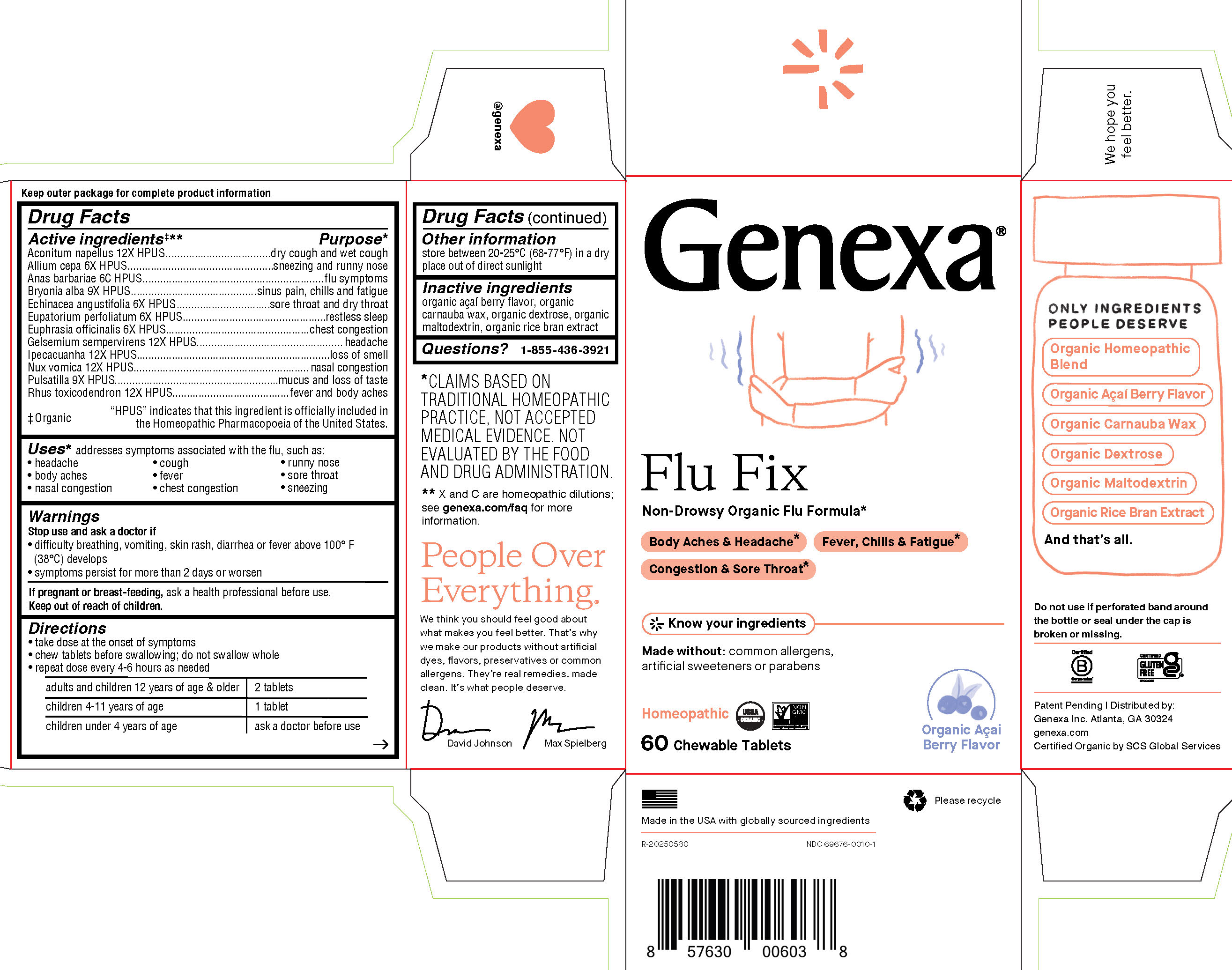 DRUG LABEL: Flu Fix
NDC: 69676-0010 | Form: TABLET, CHEWABLE
Manufacturer: Genexa Inc.
Category: homeopathic | Type: HUMAN OTC DRUG LABEL
Date: 20251215

ACTIVE INGREDIENTS: STRYCHNOS NUX-VOMICA SEED 12 [hp_X]/1 1; EUPATORIUM PERFOLIATUM FLOWERING TOP 6 [hp_X]/1 1; GELSEMIUM SEMPERVIRENS ROOT 12 [hp_X]/1 1; PULSATILLA PRATENSIS 9 [hp_X]/1 1; TOXICODENDRON PUBESCENS SHOOT 12 [hp_X]/1 1; ONION 6 [hp_X]/1 1; BRYONIA ALBA ROOT 9 [hp_X]/1 1; ECHINACEA ANGUSTIFOLIA 6 [hp_X]/1 1; ACONITUM NAPELLUS 12 [hp_X]/1 1; EUPHRASIA STRICTA 6 [hp_X]/1 1; CAIRINA MOSCHATA HEART/LIVER AUTOLYSATE 6 [hp_C]/1 1; IPECAC 12 [hp_X]/1 1
INACTIVE INGREDIENTS: DEXTROSE; RICE BRAN; CARNAUBA WAX; MALTODEXTRIN; ACAI

FLU FIX

Drug Facts

Active ingredients‡**

Aconitum napellus 12X HPUS

Allium cepa 6X HPUS

Anas barbariae 6C HPUS

Bryonia alba 9X HPUS

Echinacea angustifolia 6X HPUS

Eupatorium perfoliatum 6X HPUS

Euphrasia officinalis 6X HPUS

Gelsemium sempervirens 12X HPUS

Ipecacuanha 12X HPUS

Nux vomica 12X HPUS

Pulsatilla 9X HPUS

Rhus toxicodendron 12X HPUS

‡ Organic

"HPUS" indicates that this ingredient is officially included in the Homeopathic Pharmacopoeia of the United States.

Purpose*

dry cough and wet cough

sneezing and runny nose

flu symptoms

sinus pain, chills and fatigue

sore throat and dry throat

restless sleep

chest congestion

headache

loss of smell

nasal congestion

mucus and loss of taste

fever and body aches

Uses*

addresses symptoms associated with the flu, such as:

- headache
- cough
- runny nose
- body aches
- fever
- sore throat
- nasal congestion
- chest congestion
- sneezing

Warnings

Stop use and ask a doctorif

- difficulty breathing, vomiting, skin rash, diarrhea or fever above 100°F (38°C) develops
- symptoms persist for more than 2 days or worsen.

PREGNANCY OR BREAST FEEDING

If pregnant or breast-feeding, ask a health professional before use.

Keep out of reach of children.

Directions

- take dose at the onset of symptoms
- chew tablets before swallowing; do not swallow whole
- repeat dose every 4-6 hours as needed

adults and children 12 years of age; & older | 2 tablets
children 4-11 years of age | 1 tablet
children under 4 years of age | ask a doctor before use

Other information

store between 20-25° C (68-77° F) in a dry place out of direct sunlight

Inactive ingredients

organic açaÍ berry flavor, organic carnauba wax, organic dextrose, organic maltodextrin, organic rice bran extract

Questions?

1-855-436-3921

* CLAIMS BASED ON TRADITIONAL HOMEOPATHIC PRACTICE, NOT ACCEPTED MEDICAL EVIDENCE. NOT EVALUATED BY THE FOOD AND DRUG ADMINISTRATION.
** X and C are homeopathic dilutions: see genexa.com/faq for more information.

Do not use if perforated band around the bottle or seal under the cap is broken or missing.

Patent Pending | Distributed by:

Genexa Inc. Atlanta, GA 30324

genexa.com

Certified Organic by SCS Global Services

Made in the USA with globally sourced ingredients

NDC 69676-0010-1

PACKAGE LABEL

Genexa®

Flu Fix

Non-Drowsy Organic Flu Formula*

Body Aches & Headache*

Fever, Chills & Fatigue*

Congestion & Sore Throat*

Know your ingredients

Made without: common allergens, artificial sweeteners or parabens

Homeopathic

60 Chewable Tablets

Organic AçaÍ Berry Flavor